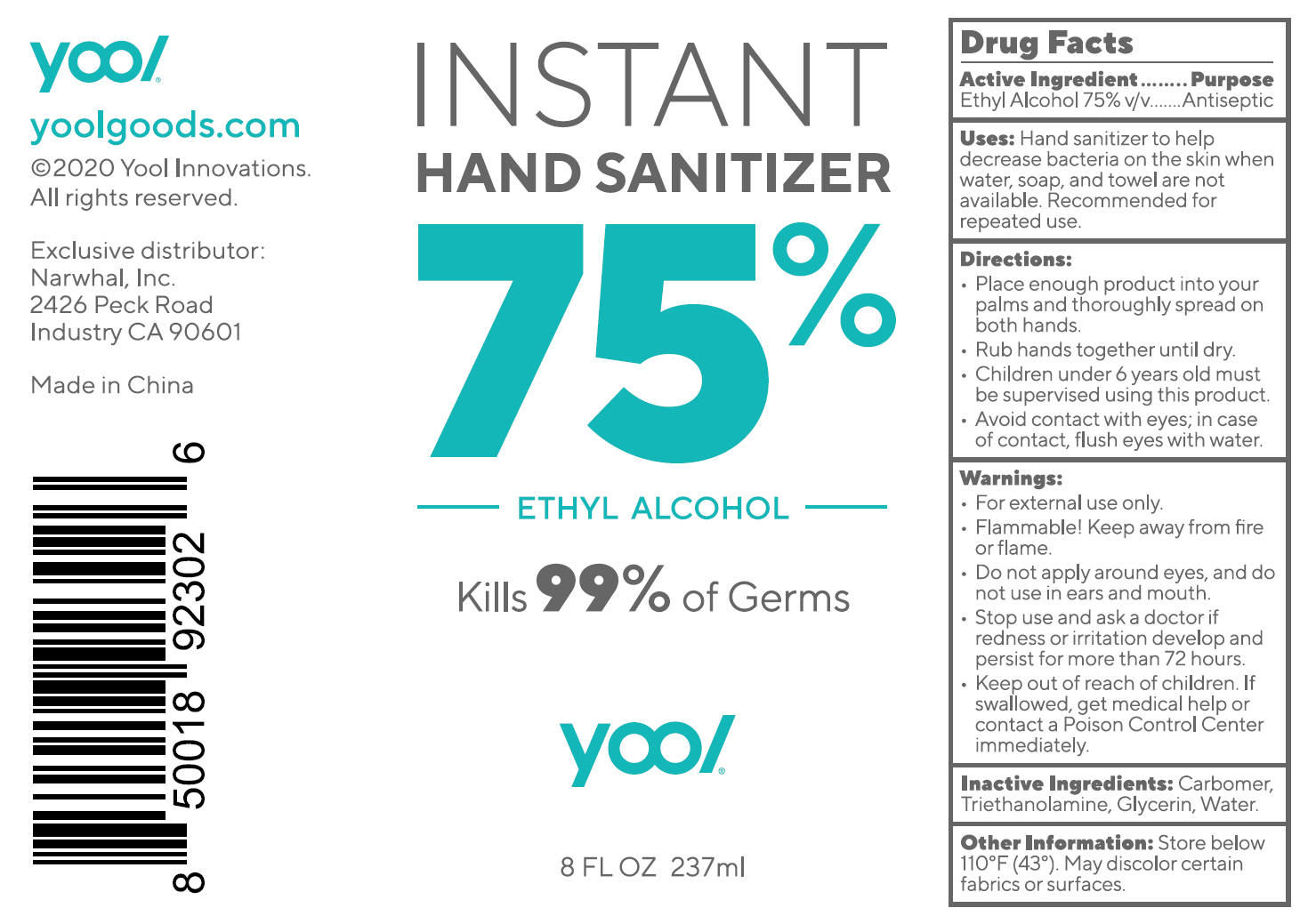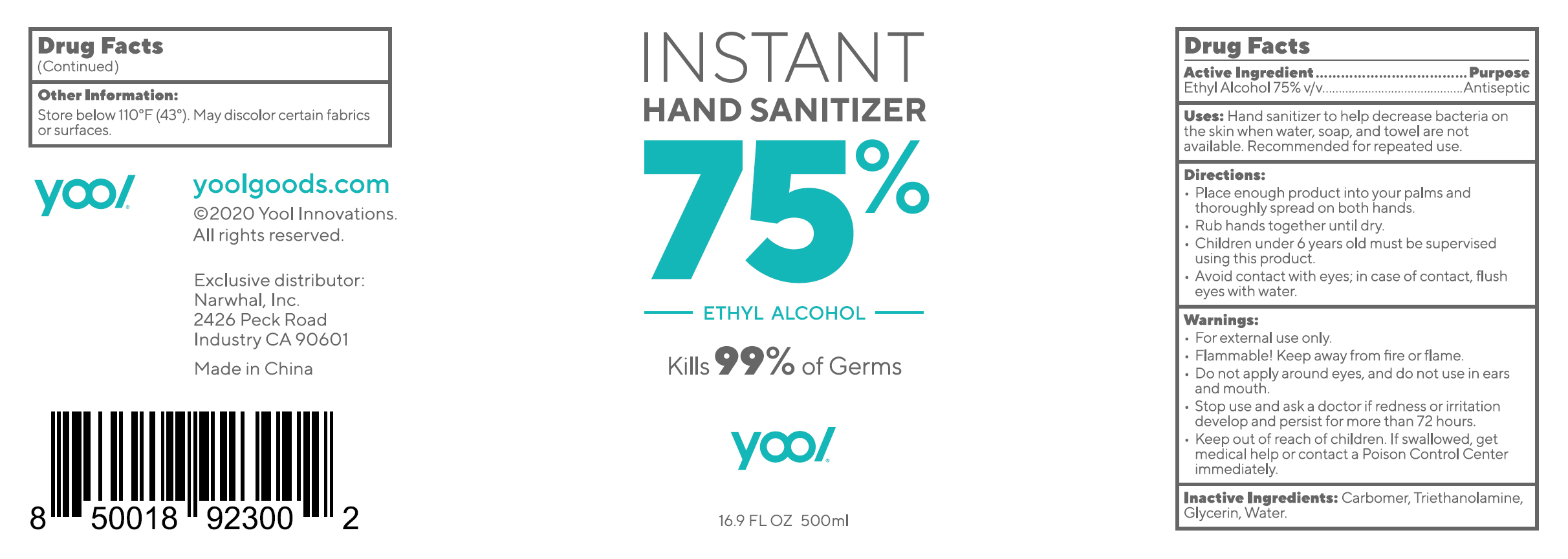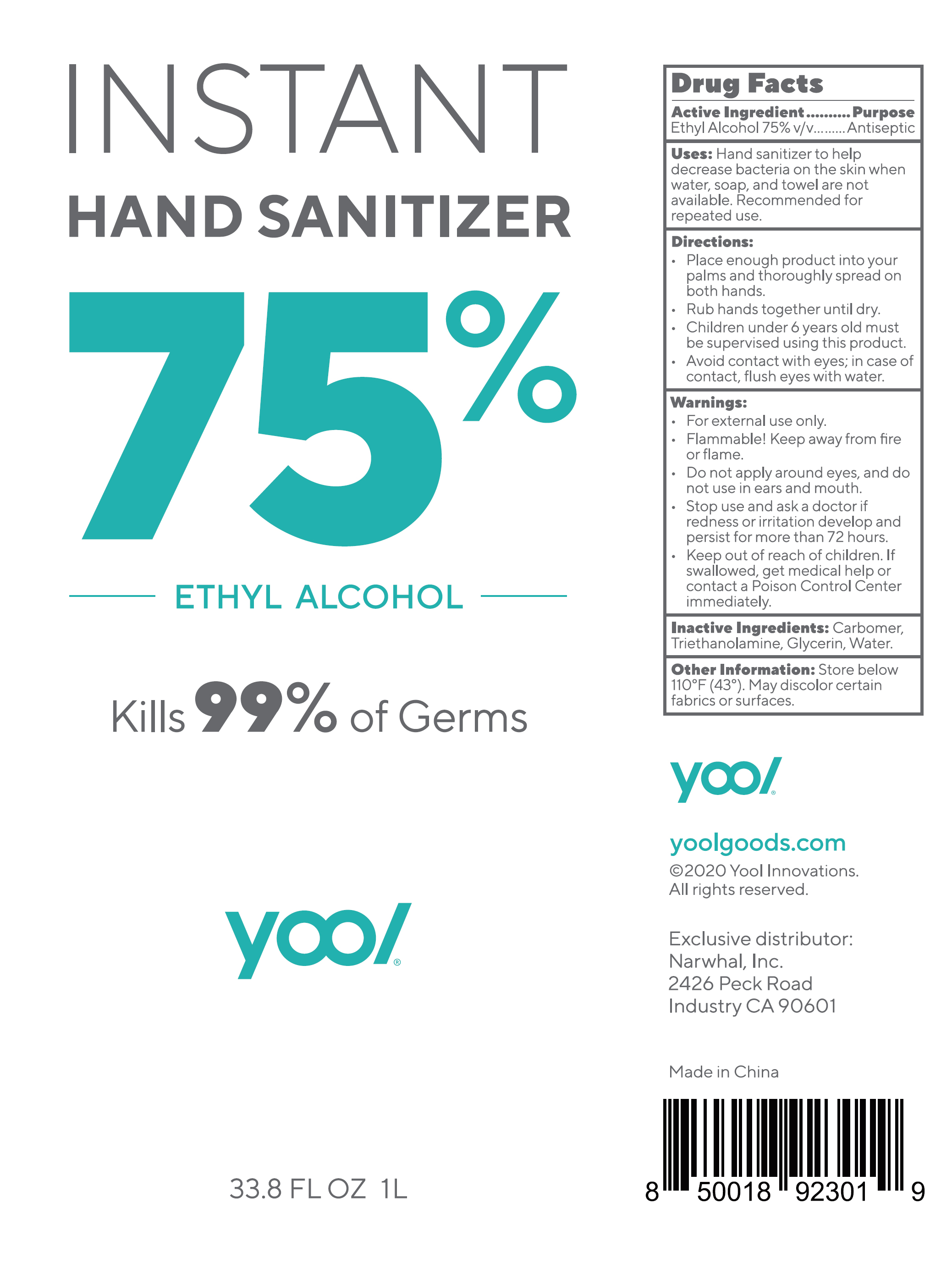 DRUG LABEL: 75% alcohol hand sanitizer
NDC: 78615-001 | Form: GEL
Manufacturer: Narwhal, Inc.
Category: otc | Type: HUMAN OTC DRUG LABEL
Date: 20230213

ACTIVE INGREDIENTS: ALCOHOL 75 mL/100 mL
INACTIVE INGREDIENTS: ACRYLIC ACID; WATER; TROLAMINE; CARBOMER HOMOPOLYMER, UNSPECIFIED TYPE

75% alcohol hand sanitizer

Active ingredient

Alcohol 75% v/v. Purpose: Antiseptic

Purpose

Antiseptic. Hand senitizer

Uses

Hand sanitizer to help decrease bacteria on the skin when water, soap, and towel are not available. Recommended for repeated use.

Directions

Place enough product into your palms and thoroughly spread on both hands.

Rub into skin until dry.

Children under 6 years old must be supervised using this product.

Avoid contact with eyes; in case of contact, flush with water.

Warnings

For external use only.

Flammable. Keep away from fire or flame.

DO NOT USE

Do not apply around eyes. Do not use in ears & mouth.

Stop use and ask a doctor if redness or irritation develop and persist for more than 72 hours.

KEEP OUT OF REACH OF CHILDREN. If swallowed, get medical help or contact a Poison Control Center immediately.

Inactive ingredients

Carbomer, triethanolamine, glycerin, water

OTHER SAFETY INFORMATION

Store below 110°F (43°C). May discolor certain fabrics or surfaces.

Package Label - Principal Display Panel

237 mL NDC: 78615-001-01

500 mL NDC: 78615-001-02

1000 mL NDC: 78615-001-03